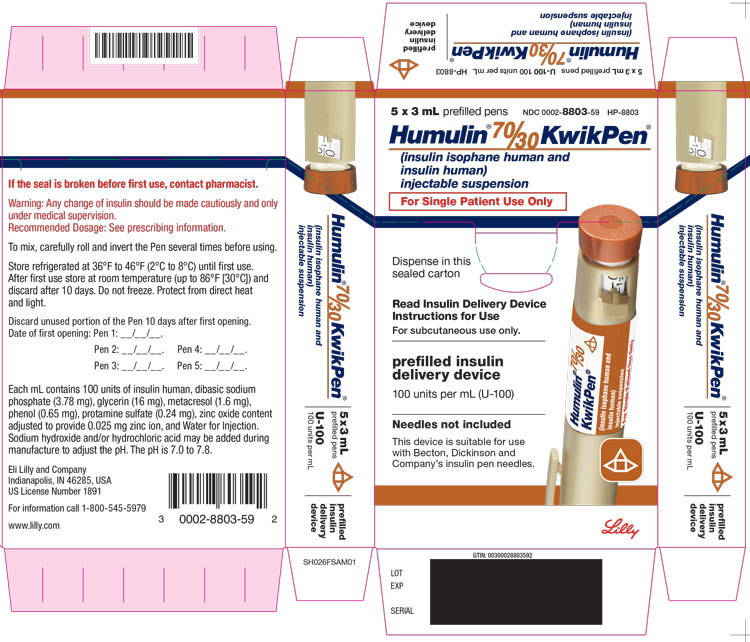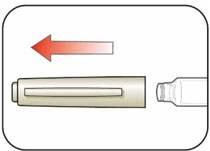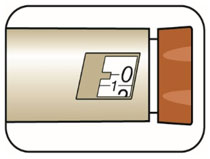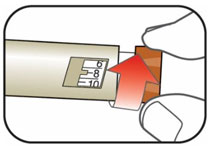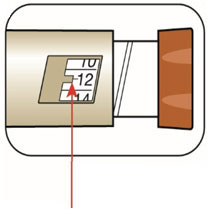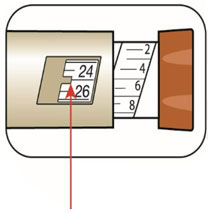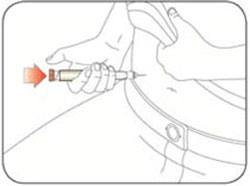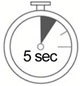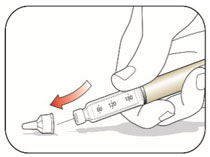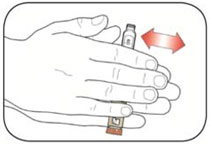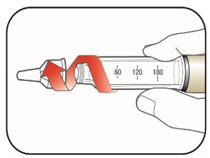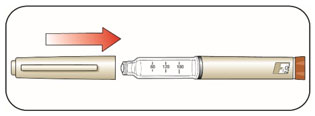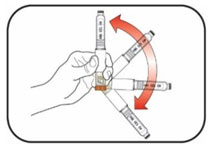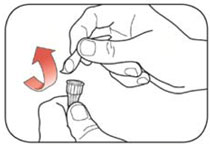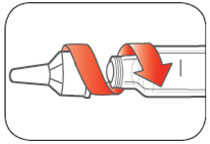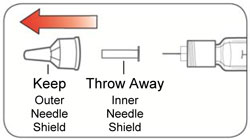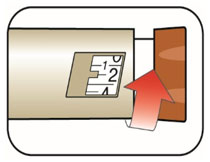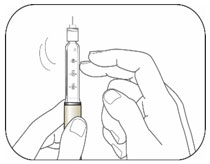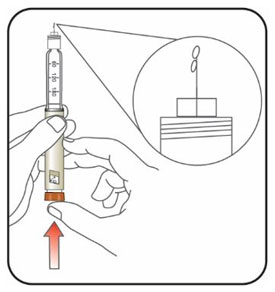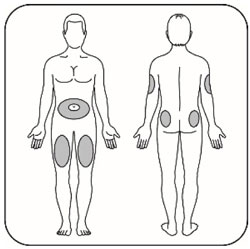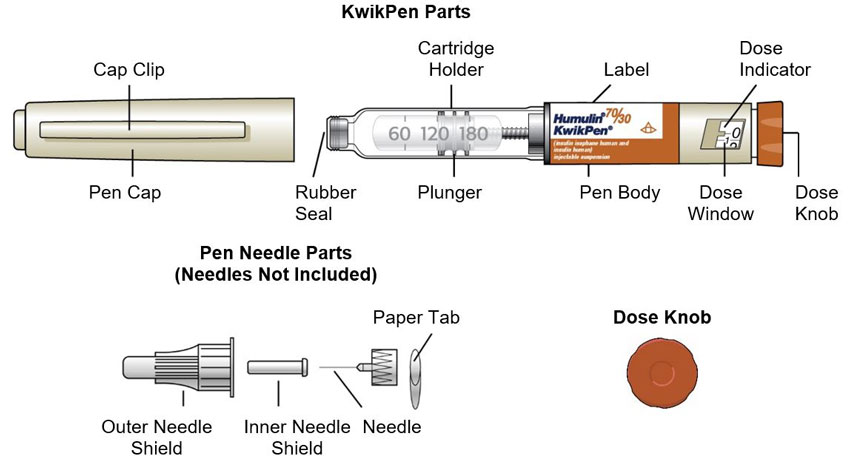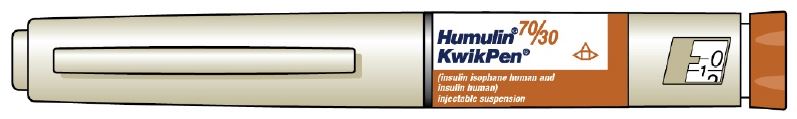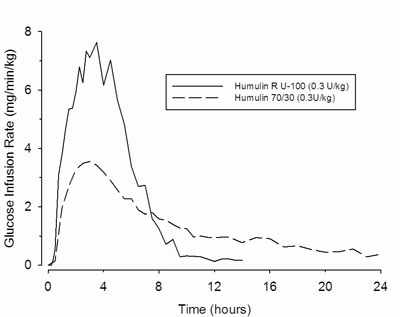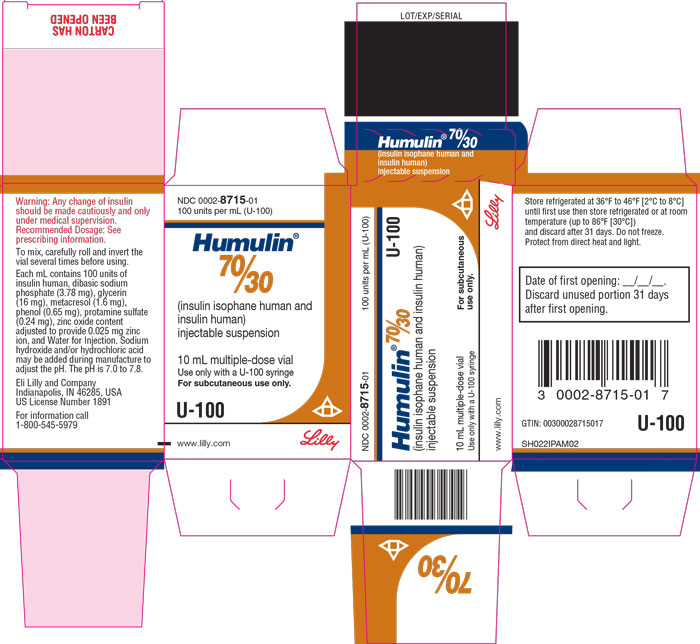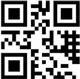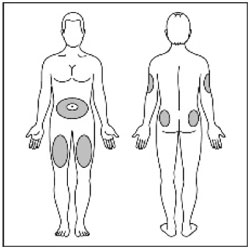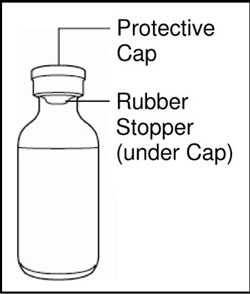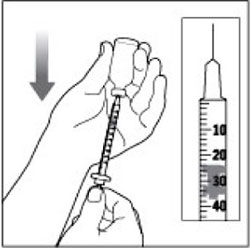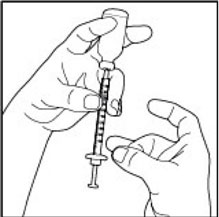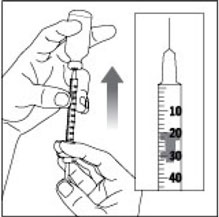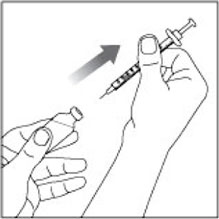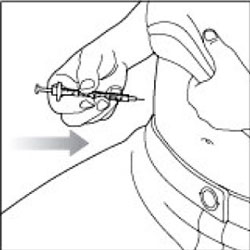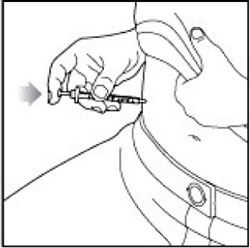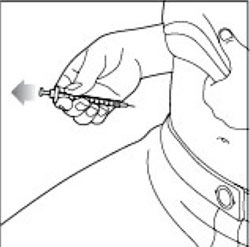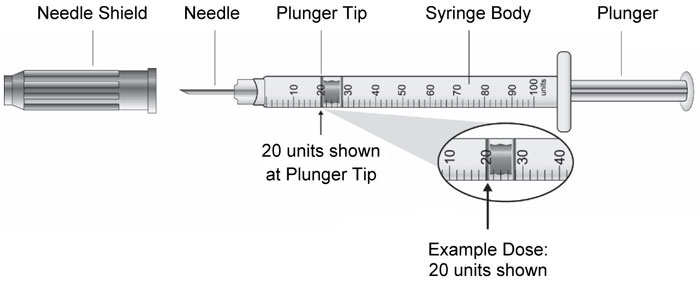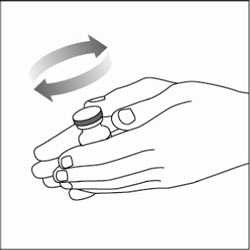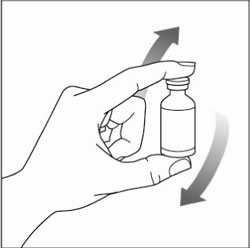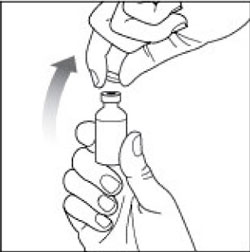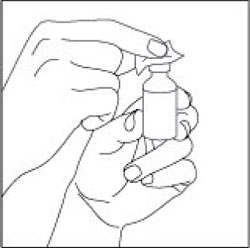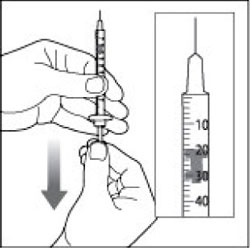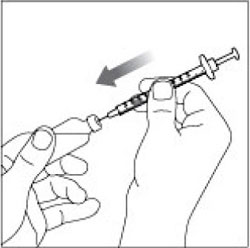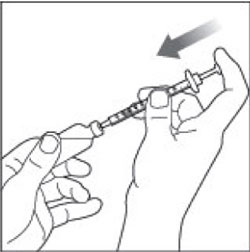 DRUG LABEL: Humulin 
NDC: 0002-8715 | Form: INJECTION, SUSPENSION
Manufacturer: Eli Lilly and Company
Category: otc | Type: HUMAN OTC DRUG LABEL
Date: 20241210

ACTIVE INGREDIENTS: Insulin human
 100 [iU]/1 mL
INACTIVE INGREDIENTS: Glycerin 16 mg/1 mL; Metacresol 1.6 mg/1 mL; Zinc 0.025 mg/1 mL; Phenol 0.65 mg/1 mL; Protamine sulfate 0.241 mg/1 mL; Sodium Phosphate, Dibasic, Heptahydrate 3.78 mg/1 mL; Water; Hydrochloric acid; Sodium hydroxide

HIGHLIGHTS OF PRESCRIBING INFORMATION

These highlights do not include all the information needed to use HUMULIN 70/30 safely and effectively. See full prescribing information for HUMULIN 70/30.
HUMULIN 70/30 (insulin isophane human and insulin human) injectable suspension, for subcutaneous use
Initial U.S. Approval: 1989

1 INDICATIONS AND USAGE

HUMULIN® 70/30 is a mixture of insulin isophane human, an intermediate-acting human insulin, and insulin human, a short-acting insulin human, indicated to improve glycemic control in adults with diabetes mellitus. (1)

2 DOSAGE AND ADMINISTRATION

- Only administer subcutaneously (in abdominal wall, thigh, upper arm, or buttocks). (2.1)
- Rotate injection sites to reduce risk of lipodystrophy and localized cutaneous amyloidosis. (2.1)
- Individualize and adjust dosage based on metabolic needs, blood glucose monitoring results and glycemic control goal. (2.2)
- See Full Prescribing Information for dosage adjustments due to drug interactions and patients with renal and hepatic impairment. (2.2)
- Administer approximately 30-45 minutes before a meal. (2.2)

3 DOSAGE FORMS AND STRENGTHS

Injectable suspension 100 units/mL (U-100) available as:

- 10 mL multiple-dose vial (3)
- 3 mL multiple-dose vial (3)
- 3 mL single-patient-use HUMULIN® 70/30 KwikPen® prefilled pen (3)

4 CONTRAINDICATIONS

- During episodes of hypoglycemia. (4)
- In patients with hypersensitivity to HUMULIN 70/30 or any of its excipients. (4)

5 WARNINGS AND PRECAUTIONS

- Never share a HUMULIN 70/30 KwikPen or syringe between patients, even if the needle is changed. (5.1)
- Hyperglycemia or Hypoglycemia with Changes in Insulin Regimen: Make changes to a patient's insulin regimen (e.g., insulin strength, manufacturer, type, injection site or method of administration) under close medical supervision with increased frequency of blood glucose monitoring. (5.2)
- Hypoglycemia: May be life-threatening. Monitor blood glucose and increase monitoring frequency with changes to insulin dosage, use of glucose lowering medications, meal pattern, physical activity; in patients with renal or hepatic impairment; and in patients with hypoglycemia unawareness. (5.3, 7, 8.6, 8.7)
- Hypoglycemia Due to Medication Errors: Accidental mix-ups between insulin products can occur. Instruct patients to check insulin labels before injection. (5.4)
- Hypersensitivity Reactions: May be life-threatening. Discontinue HUMULIN 70/30, monitor and treat if indicated. (5.5)
- Hypokalemia: May be life-threatening. Monitor potassium levels in patients at risk of hypokalemia and treat if indicated. (5.6)
- Fluid Retention and Heart Failure with Concomitant Use of Thiazolidinediones (TZDs): Observe for signs and symptoms of heart failure; consider dosage reduction or discontinuation if heart failure occurs. (5.7)

6 ADVERSE REACTIONS

Adverse reactions observed with insulin therapy include hypoglycemia, allergic reactions, injection site reactions, lipodystrophy, pruritus, rash, weight gain, and edema. (6)

To report SUSPECTED ADVERSE REACTIONS, contact Eli Lilly and Company at 1-800-LillyRx (1-800-545-5979) or FDA at 1-800-FDA-1088 or www.fda.gov/medwatch.

7 DRUG INTERACTIONS

- Drugs that Affect Glucose Metabolism: Adjustment of insulin dosage may be needed. (7)
- Antiadrenergic Drugs (e.g., beta-blockers, clonidine, guanethidine, and reserpine): Signs and symptoms of hypoglycemia may be reduced or absent. (5.3, 7)

FULL PRESCRIBING INFORMATION

1 INDICATIONS AND USAGE

HUMULIN 70/30 is a fixed ratio insulin formulation indicated to improve glycemic control in adults with diabetes mellitus.

2 DOSAGE AND ADMINISTRATION

2.1 Important Administration Instructions

Inspect HUMULIN 70/30 visually before use. It should not contain particulate matter and should appear uniformly cloudy after mixing. Do not use HUMULIN 70/30 if particulate matter is seen.

- Administer HUMULIN 70/30 subcutaneously into the abdominal wall, thigh, upper arm, or buttocks. Rotate injection sites within the same region from one injection to the next to reduce the risk of lipodystrophy and localized cutaneous amyloidosis. Do not inject into areas of lipodystrophy or localized cutaneous amyloidosis [see Warnings and Precautions (5.2) and Adverse Reactions (6)].
- The HUMULIN 70/30 KwikPen dials in 1 unit increments.
- Use HUMULIN 70/30 KwikPen with caution in patients with visual impairment that may rely on audible clicks to dial their dose.
- Do not administer HUMULIN 70/30 intravenously and do not use in an insulin infusion pump.
- Do not mix HUMULIN 70/30 with any other insulins or diluents.

2.2 Dosage Information

- Inject HUMULIN 70/30 subcutaneously approximately 30-45 minutes before a meal.
- The proportion of rapid acting and long acting insulin is fixed in a premixed insulin such as HUMULIN 70/30. Independent adjustment of the basal or prandial dose is not possible when using a premixed insulin.
- Individualize and adjust the dosage of HUMULIN 70/30 based on the individual's metabolic needs, blood glucose monitoring results and glycemic control goal. Dosage adjustments may be needed with changes in physical activity, changes in meal patterns (i.e., macronutrient content or timing of food intake), changes in renal or hepatic function or during acute illness [see Warnings and Precautions (5.2, 5.3), and Use in Specific Populations (8.6, 8.7)].
- During changes to a patient's insulin regimen, increase the frequency of blood glucose monitoring [see Warnings and Precautions (5.2)].
- HUMULIN 70/30 dose requirements may change with changes in level of physical activity, meal patterns (i.e., macronutrient content or timing of food intake), during major illness, or with some coadministered drugs [see Warnings and Precautions (5.3), Drug Interactions (7), and Use in Specific Populations (8.6, 8.7)].

3 DOSAGE FORMS AND STRENGTHS

Injectable suspension: 70% insulin isophane human and 30% insulin human, 100 units/mL (U-100), white and cloudy suspension available as:

- 10 mL multiple-dose vial
- 3 mL multiple-dose vial
- 3 mL single-patient-use HUMULIN 70/30 KwikPen prefilled pen

4 CONTRAINDICATIONS

HUMULIN 70/30 is contraindicated:

- During episodes of hypoglycemia [see Warnings and Precautions (5.3)], and
- In patients who have had hypersensitivity reactions to HUMULIN 70/30 or any of its excipients [see Warnings and Precautions (5.5)].

5 WARNINGS AND PRECAUTIONS

5.1 Never Share a HUMULIN 70/30 KwikPen or Syringe Between Patients

HUMULIN 70/30 KwikPens must never be shared between patients, even if the needle is changed. Patients using HUMULIN 70/30 vials must never share needles or syringes with another person. Sharing poses a risk for transmission of blood-borne pathogens.

5.2 Hyperglycemia or Hypoglycemia with Changes in Insulin Regimen

Changes in an insulin regimen (e.g., insulin strength, manufacturer, type, injection site or method of administration) may affect glycemic control and predispose to hypoglycemia [see Warnings and Precautions (5.3)] or hyperglycemia. Repeated insulin injections into areas of lipodystrophy or localized cutaneous amyloidosis have been reported to result in hyperglycemia; and a sudden change in the injection site (to an unaffected area) has been reported to result in hypoglycemia [see Adverse Reactions (6)].

Make any changes to a patient's insulin regimen under close medical supervision with increased frequency of blood glucose monitoring. Advise patients who have repeatedly injected into areas of lipodystrophy or localized cutaneous amyloidosis to change the injection site to unaffected areas and closely monitor for hypoglycemia. For patients with type 2 diabetes, dosage adjustments of concomitant antidiabetic products may be needed.

5.3 Hypoglycemia

Hypoglycemia is the most common adverse reaction associated with insulins, including HUMULIN 70/30. Severe hypoglycemia can cause seizures, may be life-threatening or cause death. Hypoglycemia can impair concentration ability and reaction time; this may place the patient and others at risk in situations where these abilities are important (e.g., driving or operating other machinery).

Hypoglycemia can happen suddenly and symptoms may differ in each patient and change over time in the same patient. Symptomatic awareness of hypoglycemia may be less pronounced in patients with longstanding diabetes, in patients with diabetic neuropathy, in patients using medications that block the sympathetic nervous system (e.g., beta-blockers) [see Drug Interactions (7)], or in patients who experience recurrent hypoglycemia.

Risk Factors for Hypoglycemia

The risk of hypoglycemia after an injection is related to the duration of action of the insulin and, in general, is highest when the glucose lowering effect of the insulin is maximal. As with all insulins, the glucose lowering effect time course of HUMULIN 70/30 may vary in different individuals or at different times in the same individual and depends on many conditions, including the area of injection as well as the injection site blood supply and temperature [see Clinical Pharmacology (12.2)].

Other factors which may increase the risk of hypoglycemia include changes in meal pattern (e.g., macronutrient content or timing of meals), changes in level of physical activity, or changes to concomitant drugs [see Drug Interactions (7)]. Patients with renal or hepatic impairment may be at higher risk of hypoglycemia [see Use in Specific Populations (8.6, 8.7)].

Risk Mitigation Strategies for Hypoglycemia

Patients and caregivers must be educated to recognize and manage hypoglycemia. Self-monitoring of blood glucose plays an essential role in the prevention and management of hypoglycemia. In patients at higher risk for hypoglycemia and patients who have reduced symptomatic awareness of hypoglycemia, increased frequency of blood glucose monitoring is recommended.

5.4 Hypoglycemia Due to Medication Errors

Accidental mix-ups between insulin products have been reported. To avoid medication errors between HUMULIN 70/30 and other insulins, instruct patients to always check the insulin label before each injection.

5.5 Hypersensitivity Reactions

Severe, life-threatening, generalized allergy, including anaphylaxis, can occur with insulins, including HUMULIN 70/30. If hypersensitivity reactions occur, discontinue HUMULIN 70/30; treat per standard of care and monitor until symptoms and signs resolve [see Adverse Reactions (6)]. HUMULIN 70/30 is contraindicated in patients who have had hypersensitivity reactions to HUMULIN 70/30 or any of its excipients.

5.6 Hypokalemia

All insulins, including HUMULIN 70/30, cause a shift in potassium from the extracellular to intracellular space, possibly leading to hypokalemia. Untreated hypokalemia may cause respiratory paralysis, ventricular arrhythmia, and death. Monitor potassium levels in patients at risk for hypokalemia if indicated (e.g., patients using potassium-lowering medications, patients taking medications sensitive to serum potassium concentrations).

5.7 Fluid Retention and Heart Failure with Concomitant Use of PPAR-gamma Agonists

Thiazolidinediones (TZDs), which are peroxisome proliferator-activated receptor (PPAR)-gamma agonists, can cause dose-related fluid retention, when used in combination with insulin. Fluid retention may lead to or exacerbate heart failure. Patients treated with insulin, including HUMULIN 70/30, and a PPAR-gamma agonist should be observed for signs and symptoms of heart failure. If heart failure develops, it should be managed according to current standards of care, and discontinuation or dose reduction of the PPAR-gamma agonist must be considered.

6 ADVERSE REACTIONS

The following adverse reactions are discussed elsewhere in the labeling:

- Hypoglycemia [see Warnings and Precautions (5.3)].
- Hypoglycemia Due to Medication Errors [see Warnings and Precautions (5.4)].
- Hypersensitivity Reactions [see Warnings and Precautions (5.5)].
- Hypokalemia [see Warnings and Precautions (5.6)].

The following additional adverse reactions have been identified during post-approval use of HUMULIN 70/30. Because these reactions are reported voluntarily from a population of uncertain size, it is not always possible to reliably estimate their frequency or to establish a causal relationship to drug exposure.

Allergic Reactions

Some patients taking HUMULIN 70/30 have experienced erythema, local edema, and pruritus at the site of injection. These conditions were usually self-limiting. Severe cases of generalized allergy (anaphylaxis) have been reported [see Warnings and Precautions (5.5)].

Peripheral Edema

Some patients taking HUMULIN 70/30 have experienced sodium retention and edema, particularly if previously poor metabolic control is improved by intensified insulin therapy.

Lipodystrophy

Administration of insulin subcutaneously, including HUMULIN 70/30, has resulted in lipoatrophy (depression in the skin) or lipohypertrophy (enlargement or thickening of tissue) [see Dosage and Administration (2.1)] in some patients.

Localized Cutaneous Amyloidosis

Localized cutaneous amyloidosis at the injection site has occurred. Hyperglycemia has been reported with repeated insulin injections into areas of localized cutaneous amyloidosis; hypoglycemia has been reported with a sudden change to an unaffected injection site.

Weight gain

Weight gain has occurred with insulins, including HUMULIN 70/30, and has been attributed to the anabolic effects of insulin and the decrease in glycosuria.

Immunogenicity

Development of antibodies that react with human insulin have been observed with all insulins, including HUMULIN 70/30.

7 DRUG INTERACTIONS

Table 1: Clinically Significant Drug Interactions with HUMULIN 70/30
Drugs that May Increase the Risk of Hypoglycemia
Drugs: | Antidiabetic agents, ACE inhibitors, angiotensin II receptor blocking agents, disopyramide, fibrates, fluoxetine, monoamine oxidase inhibitors, pentoxifylline, pramlintide, salicylates, somatostatin analog (e.g., octreotide), and sulfonamide antibiotics
Intervention: | Dose adjustment and increased frequency of glucose monitoring may be required when HUMULIN 70/30 is co-administered with these drugs.
Drugs that May Decrease the Blood Glucose Lowering Effect of HUMULIN 70/30
Drugs: | Atypical antipsychotics (e.g., olanzapine and clozapine), corticosteroids, danazol, diuretics, estrogens, glucagon, isoniazid, niacin, oral contraceptives, phenothiazines, progestogens (e.g., in oral contraceptives), protease inhibitors, somatropin, sympathomimetic agents (e.g., albuterol, epinephrine, terbutaline), and thyroid hormones.
Intervention: | Dose adjustment and increased frequency of glucose monitoring may be required when HUMULIN 70/30 is co-administered with these drugs.
Drugs that May Increase or Decrease the Blood Glucose Lowering Effect of HUMULIN 70/30
Drugs: | Alcohol, beta-blockers, clonidine, and lithium salts. Pentamidine may cause hypoglycemia, which may sometimes be followed by hyperglycemia.
Intervention: | Dose adjustment and increased frequency of glucose monitoring may be required when HUMULIN 70/30 is co-administered with these drugs.
Drugs that May Blunt Signs and Symptoms of Hypoglycemia
Drugs: | Beta-blockers, clonidine, guanethidine, and reserpine
Intervention: | Increased frequency of glucose monitoring may be required when HUMULIN 70/30 is co-administered with these drugs.

8 USE IN SPECIFIC POPULATIONS

8.1 Pregnancy

Risk Summary

Available data from published studies over decades have not established an association with human insulin use during pregnancy and major birth defects, miscarriage, or adverse maternal or fetal outcomes (see Data). There are risks to the mother and fetus associated with poorly controlled diabetes in pregnancy (see Clinical Considerations). Animal reproduction studies were not performed.

The estimated background risk of major birth defects is 6-10% in women with pre-gestational diabetes with a HbA1c >7% and has been reported to be as high as 20-25% in women with a HbA1c >10%. The estimated background risk of miscarriage for the indicated population is unknown. In the U.S. general population, the estimated background risk of major birth defects and miscarriage in clinically recognized pregnancies is 2-4% and 15-20%, respectively.

Clinical Considerations

Disease-associated maternal and/or embryo/fetal risk

Poorly controlled diabetes in pregnancy increases the maternal risk for diabetic ketoacidosis, pre-eclampsia, spontaneous abortions, preterm delivery, and delivery complications. Poorly controlled diabetes increases the fetal risk for major birth defects, stillbirth, and macrosomia-related morbidity.

Data

Human Data

While available studies cannot definitively establish the absence of risk, published data from retrospective studies, open-label, randomized, parallel studies and meta-analyses over decades have not established an association with human insulin use during pregnancy and major birth defects, miscarriage, or adverse maternal or fetal outcomes. All available studies have methodological limitations, including lack of blinding, unclear methods or randomization, and small sample size.

8.2 Lactation

Risk Summary

Available data from published literature suggests that exogenous human insulin products, including HUMULIN 70/30, are transferred into human milk. There are no adverse reactions reported in breastfed infants in the literature. There are no data on the effects of exogenous human insulin products, including HUMULIN 70/30 on milk production. The developmental and health benefits of breastfeeding should be considered along with the mother's clinical need for HUMULIN 70/30 and any potential adverse effects on the breastfed child from HUMULIN 70/30 or from the underlying maternal condition.

8.4 Pediatric Use

The safety and effectiveness of HUMULIN 70/30 in pediatric patients have not been established.

8.5 Geriatric Use

The effect of age on the pharmacokinetics and pharmacodynamics of HUMULIN 70/30 has not been studied [see Clinical Pharmacology (12.3)]. Patients with advanced age using any insulin, including HUMULIN 70/30, may be at increased risk of hypoglycemia due to co-morbid disease and polypharmacy [see Warnings and Precautions (5.3)].

8.6 Renal Impairment

The effect of renal impairment on the pharmacokinetics and pharmacodynamics of HUMULIN 70/30 has not been studied [see Clinical Pharmacology (12.3)]. Patients with renal impairment are at increased risk of hypoglycemia and may require more frequent HUMULIN 70/30 dose adjustment and more frequent blood glucose monitoring.

8.7 Hepatic Impairment

The effect of hepatic impairment on the pharmacokinetics and pharmacodynamics of HUMULIN 70/30 has not been studied [see Clinical Pharmacology (12.3)]. Patients with hepatic impairment are at increased risk of hypoglycemia and may require more frequent HUMULIN 70/30 dose adjustment and more frequent blood glucose monitoring.

10 OVERDOSAGE

Excess insulin administration may cause hypoglycemia and hypokalemia [see Warnings and Precautions (5.3, 5.6)]. Mild episodes of hypoglycemia can be treated with oral glucose. Adjustments in drug dosage, meal patterns, or physical activity level may be needed. More severe episodes with coma, seizure, or neurologic impairment may be treated with a glucagon product for emergency use or concentrated intravenous glucose. Sustained carbohydrate intake and observation may be necessary because hypoglycemia may recur after apparent clinical recovery. Hypokalemia must be corrected appropriately.

11 DESCRIPTION

Insulin human is produced by recombinant DNA technology utilizing a non-pathogenic laboratory strain of Escherichia coli. The amino acid sequence of insulin human is identical to human insulin and has the empirical formula C257H383N65O77S6 with a molecular weight of 5.808 kDa.

HUMULIN 70/30 (insulin isophane human and insulin human) injectable suspension is a mixture of 70% insulin isophane human suspension, an intermediate-acting insulin, and 30% insulin human injection, a short-acting insulin. HUMULIN 70/30 is a suspension of crystals produced from combining insulin human and protamine sulfate under appropriate conditions for crystal formation and mixing with insulin human injection.

HUMULIN 70/30 is a sterile, white and cloudy suspension that contains insulin isophane human suspension (NPH) and insulin human injection (regular) for subcutaneous use. Each milliliter of HUMULIN 70/30 contains 100 units of insulin human, dibasic sodium phosphate (3.78 mg), glycerin (16 mg), metacresol (1.6 mg), phenol (0.65 mg), protamine sulfate (0.24 mg), zinc oxide content adjusted to provide 0.025 mg zinc ion, and Water for Injection. The pH is 7.0 to 7.8. Sodium hydroxide and/or hydrochloric acid may be added during manufacture to adjust the pH.

12 CLINICAL PHARMACOLOGY

12.1 Mechanism of Action

HUMULIN 70/30 lowers blood glucose by stimulating peripheral glucose uptake by skeletal muscle and fat, and by inhibiting hepatic glucose production. Insulins inhibit lipolysis and proteolysis, and enhance protein synthesis.

12.2 Pharmacodynamics

HUMULIN 70/30 combines an intermediate-acting insulin with the more rapid onset of action of regular human insulin. In healthy males (n=18) given HUMULIN 70/30 (0.3 unit/kg) subcutaneously, the pharmacologic effect began at approximately 50 minutes (range: 30 to 90 minutes) (see Figure 1). The effect was maximal at approximately 3.5 hours (range: 1.5 to 6.5 hours) and the mean duration of action was relatively long (approximately 23 hours; range: 18-24 hours).

Figure 1 should be considered only as a representative example since the time course of action of insulin may vary in different individuals or within the same individual. The rate of insulin absorption and consequently the onset of activity is known to be affected by the site of injection, physical activity level, and other variables [see Warnings and Precautions (5.3)].

Figure 1: Mean Insulin Activity Versus Time Profiles After Subcutaneous Injection of HUMULIN 70/30 or HUMULIN® R U‑100 (0.3 unit/kg) in Healthy Subjects.

12.3 Pharmacokinetics

Absorption — In healthy male subjects given HUMULIN 70/30 (0.3 unit/kg) subcutaneously, the mean peak serum concentration occurred at 2.2 hours (range: 1 to 5 hours) after dosing.

Metabolism — The uptake and degradation of insulin occurs predominantly in liver, kidney, muscle, and adipocytes, with the liver being the major organ involved in the clearance of insulin.

Elimination — Because of the absorption-rate limited kinetics of insulin mixtures, a true half-life cannot be accurately estimated from the terminal slope of the concentration versus time curve.

Specific Populations

The effects of age, gender, race, obesity, pregnancy, or smoking on the pharmacokinetics of HUMULIN 70/30 have not been studied.

13 NONCLINICAL TOXICOLOGY

13.1 Carcinogenesis, Mutagenesis, Impairment of Fertility

Carcinogenicity and fertility studies were not performed in animals. Biosynthetic human insulin was not genotoxic in the in vivo sister chromatid exchange assay and the in vitro gradient plate and unscheduled DNA synthesis assays.

16 HOW SUPPLIED/STORAGE AND HANDLING

16.1 How Supplied

HUMULIN 70/30 (insulin isophane human and insulin human) injectable suspension is 70% insulin isophane human and 30% insulin human, 100 units/mL (U-100), a white and cloudy suspension available as:

10 mL multiple-dose vial | NDC 0002-8715-01 (HI-710)
3 mL multiple-dose vial | NDC 0002-8715-17 (HI-713)
5 x 3 mL single-patient-use HUMULIN 70/30 KwikPen | NDC 0002-8803-59 (HP-8803)

Each prefilled HUMULIN 70/30 KwikPen is for use by a single patient. HUMULIN 70/30 KwikPens must never be shared between patients, even if the needle is changed. Patients using HUMULIN 70/30 vials must never share needles or syringes with another person.

The HUMULIN 70/30 KwikPen dials in 1 unit increments.

16.2 Storage and Handling

Dispense in the original sealed carton with the enclosed Instructions for Use.

Protect from heat and light. Do not freeze. Do not use if it has been frozen. See Table 2 below for storage conditions.

Table 2: Storage Conditions for HUMULIN 70/30 Vials and Pens
 | Not In-use (Unopened) |  | In-use (Opened)
 | Room Temperature (up to 86°F [30°C]) | Refrigerated (36° to 46°F [2° to 8°C]) | Room Temperature (up to 86°F [30°C]) | Refrigerated (36° to 46°F [2° to 8°C])
10 mL multiple-dose viala 3 mL multiple-dose viala | 31 days | Until expiration date | 31 days | 31 days
3 mL single-patient-use HUMULIN 70/30 KwikPenb | 10 days | Until expiration date | 10 days | Do not refrigerate.
a When stored at room temperature, HUMULIN 70/30 vial can only be used for a total of 31 days including both not in-use (unopened) and in-use (opened) storage time.
b When stored at room temperature, HUMULIN 70/30 KwikPen can only be used for a total of 10 days including both not in-use (unopened) and in-use (opened) storage time.

17 PATIENT COUNSELING INFORMATION

Advise the patient to read the FDA-approved patient labeling (Patient Information and Instructions for Use).

Never Share a HUMULIN 70/30 KwikPen or Syringe Between Patients

Advise patients that they must never share a HUMULIN 70/30 KwikPen with another person, even if the needle is changed. Advise patients using HUMULIN 70/30 vials not to share needles or syringes with another person. Sharing poses a risk for transmission of blood-borne pathogens [see Warnings and Precautions (5.1)].

Hyperglycemia or Hypoglycemia

Instruct patients on self-management procedures including glucose monitoring, proper injection technique, and management of hypoglycemia and hyperglycemia especially at initiation of HUMULIN 70/30 therapy. Instruct patients on handling of special situations such as intercurrent conditions (illness, stress, or emotional disturbances), an inadequate or skipped insulin dose, inadvertent administration of an increased insulin dose, inadequate food intake, and skipped meals. Instruct patients on the management of hypoglycemia.

Inform patients that their ability to concentrate and react may be impaired as a result of hypoglycemia. Advise patients who have frequent hypoglycemia or reduced or absent warning signs of hypoglycemia to use caution when driving or operating machinery [see Warnings and Precautions (5.3)].

Advise patients that changes in insulin regimen can predispose to hyperglycemia or hypoglycemia and that changes in insulin regimen should be made under close medical supervision [see Warnings and Precautions (5.2)].

Inform patients that accidental mix-ups between insulin products have been reported. Instruct patients to always carefully check that they are administering the correct insulin (e.g., by checking the insulin label before each injection) to avoid medication errors between HUMULIN 70/30 and other insulins.

Hypersensitivity Reactions

Advise patients that hypersensitivity reactions have occurred with HUMULIN 70/30. Inform patients on the symptoms of hypersensitivity reactions [see Warnings and Precautions (5.5)].

____________

HUMULIN® and HUMULIN® 70/30 KwikPen® are trademarks of Eli Lilly and Company.

Literature revised June 2022

Manufactured by:
Eli Lilly and Company
Indianapolis, IN 46285, USA
US License Number 1891
Copyright © 1992, 2022, Eli Lilly and Company. All rights reserved.

LIN7030-0006-USPI-20220627

PATIENT INFORMATION
HUMULIN® (HU-mu-lin) 70/30
(insulin isophane human and insulin human)
injectable suspension, for subcutaneous use

Do not share your HUMULIN 70/30 KwikPen or syringes with other people, even if the needle has been changed. You may give other people a serious infection or get a serious infection from them.

What is HUMULIN 70/30?

- HUMULIN 70/30 is a man-made insulin that is used to control high blood sugar in adults with diabetes mellitus.

Who should not use HUMULIN 70/30?

Do not use HUMULIN 70/30 if you:

- are having an episode of low blood sugar (hypoglycemia).
- have an allergy to HUMULIN 70/30 or any of the ingredients in HUMULIN 70/30.

Before using HUMULIN 70/30, tell your healthcare provider about all your medical conditions including, if you:

- have liver or kidney problems.
- take any other medicines, especially ones commonly called TZDs (thiazolidinediones).
- have heart failure or other heart problems. If you have heart failure, it may get worse while you take TZDs with HUMULIN 70/30.
- are pregnant, planning to become pregnant. Talk with your healthcare provider about the best way to control your blood sugar if you plan to become pregnant or while you are pregnant.
- are breast-feeding or plan to breastfeed. HUMULIN 70/30 may pass into your breast milk. Talk with your healthcare provider about the best way to feed your baby while using HUMULIN 70/30.
- are taking new prescription or over-the-counter medicines, vitamins, or herbal supplements.

Before you start using HUMULIN 70/30, talk to your healthcare provider about low blood sugar and how to manage it.

How should I use HUMULIN 70/30?

- Read the Instructions for Use that come with your HUMULIN 70/30.
- Use HUMULIN 70/30 exactly as your healthcare provider tells you to. HUMULIN 70/30 is injected under the skin (subcutaneously) of your stomach area, buttocks, upper legs or upper arms. Change (rotate) your injection sites within the area you choose with each dose to reduce your risk of getting lipodystrophy (pits in skin or thickened skin) and localized cutaneous amyloidosis (skin with lumps) at the injection sites. Do not use the exact same spot for each injection. Do not inject where the skin has pits, is thickened, or has lumps. Do not inject where the skin is tender, bruised, scaly or hard, or into scars or damaged skin.
- Know the type and strength of insulin you use. Do not change the type of insulin you use unless your healthcare provider tells you to. The amount of insulin and the best time for you to take your insulin may need to change if you use different types of insulin.
- Check your blood sugar levels. Ask your healthcare provider what your blood sugars should be and when you should check your blood sugar levels.
- Do not share your HUMULIN 70/30 KwikPen or syringes with other people, even if the needle has been changed. You may give other people a serious infection or get a serious infection from them.

Your HUMULIN 70/30 dose may need to change because of:

- change in level of physical activity or exercise, weight gain or loss, increased stress, illness, change in diet.

What should I avoid while using HUMULIN 70/30?

While using HUMULIN 70/30 do not:

- drive or operate heavy machinery, until you know how HUMULIN 70/30 affects you.
- drink alcohol or use prescription or over-the-counter medicines that contain alcohol.

What are the possible side effects of HUMULIN 70/30?

HUMULIN 70/30 may cause serious side effects that can lead to death, including:

- low blood sugar (hypoglycemia). Signs and symptoms that may indicate low blood sugar include:
  - dizziness or light-headedness, sweating, confusion, headache, blurred vision, slurred speech, shakiness, fast heartbeat, anxiety, irritability, or mood changes, hunger.
- serious allergic reaction (whole body reaction). Get medical help right away, if you have any of these symptoms of an allergic reaction:
  - a rash over your whole body, trouble breathing, a fast heartbeat, or sweating.
- low potassium in your blood (hypokalemia).
- heart failure. Taking certain diabetes pills called thiazolidinediones or “TZDs” with HUMULIN 70/30 may cause heart failure in some people. This can happen even if you have never had heart failure or heart problems before. If you already have heart failure it may get worse while you take TZDs with HUMULIN 70/30. Your healthcare provider should monitor you closely while you are taking TZDs with HUMULIN 70/30. Tell your healthcare provider if you have any new or worse symptoms of heart failure including:
  - shortness of breath, swelling of your ankles or feet, sudden weight gain.
    Treatment with TZDs and HUMULIN 70/30 may need to be adjusted or stopped by your healthcare provider if you have new or worse heart failure.

Get emergency medical help if you have:

- trouble breathing, shortness of breath, fast heartbeat, swelling of your face, tongue, or throat, sweating, extreme drowsiness, dizziness, confusion.

The most common side effects of HUMULIN 70/30 include:

- low blood sugar (hypoglycemia), allergic reactions including reactions at the injection site, skin thickening or pits at the injection site (lipodystrophy), itching, rash, weight gain, and swelling of your hands and feet. These are not all the possible side effects of HUMULIN 70/30. Call your doctor for medical advice about side effects. You may report side effects to FDA at 1-800-FDA-1088.

General information about the safe and effective use of HUMULIN 70/30:

Medicines are sometimes prescribed for purposes other than those listed in a Patient Information leaflet. You can ask your pharmacist or healthcare provider for information about HUMULIN 70/30 that is written for health professionals. Do not use HUMULIN 70/30 for a condition for which it was not prescribed. Do not give HUMULIN 70/30 to other people, even if they have the same symptoms that you have. It may harm them.

What are the ingredients in HUMULIN 70/30?

Active Ingredient: insulin human

Inactive Ingredients: dibasic sodium phosphate, glycerin, metacresol, phenol, protamine sulfate, zinc oxide, and Water for Injection as inactive ingredients. Sodium hydroxide and/or hydrochloric acid may be added to adjust the pH.

For more information, call 1-800-545-5979 or go to www.humulin.com.

This Patient Information has been approved by the U.S. Food and Drug Administration.

Patient Information revised June 2022

Manufactured by:
Eli Lilly and Company, Indianapolis, IN 46285, USA
US License Number 1891
Copyright © 1992, 2022, Eli Lilly and Company. All rights reserved.

LIN7030-0005-PPI-20220627

VIAL INSTRUCTIONS FOR USE

Instructions for Use
HUMULIN® (HU-mu-lin) 70/30
(insulin isophane human and insulin human)
injectable suspension, for subcutaneous use
3 mL or 10 mL multiple-dose vial (100 units/mL)

Read the Instructions for Use before you start taking HUMULIN 70/30 and each time you get a new HUMULIN 70/30 vial. There may be new information. This information does not take the place of talking to your healthcare provider about your medical condition or your treatment.

Do not share your syringes with other people, even if the needle has been changed. You may give other people a serious infection or get a serious infection from them.

Supplies needed to give your injection:

- a 3 mL or 10 mL multiple-dose HUMULIN 70/30 vial
- a U-100 insulin syringe and needle
- 2 alcohol swabs
- 1 sharps container for throwing away used needles and syringes. See “Disposing of used needles and syringes” at the end of these instructions.

Vial

Syringe

Preparing your HUMULIN 70/30 dose:

- Wash your hands with soap and water.
- Check the HUMULIN 70/30 label to make sure you are taking the right type of insulin. This is especially important if you use more than 1 type of insulin.
- Do not use HUMULIN 70/30 past the expiration date printed on the label or 31 days after you first use it.
- Always use a new syringe or needle for each injection to help ensure sterility and prevent blocked needles. Do not reuse or share your syringes or needles with other people. You may give other people a serious infection or get a serious infection from them.

Step 1:
Gently roll the vial between the palms of your hands at least 10 times.

Step 2:
Carefully invert the vial at least 10 times.
Mixing is important to make sure you get the right dose. Humulin 70/30 should look white and cloudy after mixing. Do not use it if it looks clear or contains any lumps or particles.

Step 3:
If you are using a new vial, pull off the plastic Protective Cap, but do not remove the Rubber Stopper.

Step 4:
Wipe the Rubber Stopper with an alcohol swab.

Step 5:
Hold the syringe with the needle pointing up. Pull down on the Plunger until the tip of the Plunger reaches the line for the number of units for your prescribed dose.

(Example Dose: 20 units shown)

Step 6:
Push the needle through the Rubber Stopper of the vial.

Step 7:
Push the plunger all the way in. This puts air into the vial.

Step 8:
Turn the vial and syringe upside down and slowly pull the Plunger down until the tip is a few units past the line for your prescribed dose.
If there are air bubbles, tap the syringe gently a few times to let any air bubbles rise to the top.

(Example Dose: 20 units Plunger is shown at 24 units)

Step 9:
Slowly push the Plunger up until the tip reaches the line for your prescribed dose.
Check the syringe to make sure that you have the right dose.

(Example Dose: 20 units shown)

Step 10:
Pull the syringe out of the vial's Rubber Stopper.

Giving your HUMULIN 70/30 injection:

- Inject your insulin exactly as your healthcare provider has shown you.
- Change (rotate) your injection sites within the area you choose for each dose to reduce your risk of getting lipodystrophy (pits in skin or thickened skin) and localized cutaneous amyloidosis (skin with lumps) at the injection sites. Do not inject where the skin has pits, is thickened, or has lumps. Do not inject where the skin is tender, bruised, scaly or hard, or into scars or damaged skin.

Step 11:
Choose your injection site.
HUMULIN 70/30 is injected under the skin (subcutaneously) of your stomach area (abdomen), buttocks, upper legs or upper arms.
Wipe the skin with an alcohol swab. Let the injection site dry before you inject your dose.

Step 12:
Insert the needle into your skin.

Step 13:
Push down on the Plunger to inject your dose.
The needle should stay in your skin for at least 5 seconds to make sure you have injected all of your insulin dose.

Step 14:
Pull the needle out of your skin.

- If you see blood after you take the needle out of your skin, press the injection site with a piece of gauze or an alcohol swab. Do not rub the area.
- Do not recap the needle. Recapping the needle can lead to a needle stick injury.

Disposing of used needles and syringes:

- Put your used needles and syringes in a FDA-cleared sharps disposal container right away after use. Do not throw away (dispose of) loose needles and syringes in your household trash.
- If you do not have a FDA-cleared sharps disposal container, you may use a household container that is:
  - made of a heavy-duty plastic,
  - can be closed with a tight-fitting, puncture-resistant lid, without sharps being able to come out,
  - upright and stable during use,
  - leak-resistant, and
  - properly labeled to warn of hazardous waste inside the container.
- When your sharps disposal container is almost full, you will need to follow your community guidelines for the right way to dispose of your sharps disposal container. There may be state or local laws about how you should throw away used needles and syringes. For more information about safe sharps disposal, and for specific information about sharps disposal in the state that you live in, go to the FDA's website at: http://www.fda.gov/safesharpsdisposal.
- Do not dispose of your used sharps disposal container in your household trash unless your community guidelines permit this. Do not recycle your used sharps disposal container.

How should I store HUMULIN 70/30?

All unopened HUMULIN 70/30 vials:

- Store all unopened vials in the refrigerator.
- Do not freeze. Do not use if it has been frozen.
- Keep away from heat and out of direct light.
- Unopened vials can be used until the expiration date on the carton and label, if they have been stored in the refrigerator.
- Unopened vials should be thrown away after 31 days, if they are stored at room temperature.

After HUMULIN 70/30 vials have been opened:

- Store opened vials in the refrigerator or at room temperature up to 86°F (30°C) for up to 31 days.
- Keep away from heat and out of direct light.
- Throw away all opened vials after 31 days of use, even if there is still insulin left in the vial.

General information about the safe and effective use of HUMULIN 70/30.

- Keep HUMULIN 70/30 vials, syringes, needles, and all medicines out of the reach of children.
- Always use a new syringe or needle for each injection.
- Do not reuse or share your syringes or needles with other people. You may give other people a serious infection or get a serious infection from them.

If you have any questions or problems with your HUMULIN, contact Lilly at 1-800-Lilly-Rx (1-800-545-5979) or call your healthcare provider for help. For more information on HUMULIN and insulin, go to www.humulin.com.

Scan this code to launch the humulin.com website

This Instructions for Use has been approved by the U.S. Food and Drug Administration.

Humulin® is a trademark of Eli Lilly and Company.

Instructions for Use revised: June 2022

Manufactured by:
Eli Lilly and Company, Indianapolis, IN 46285, USA
US License Number 1891
Copyright © 1992, 2022, Eli Lilly and Company. All rights reserved.

LIN7030VL-0005-IFU-20220627

KWIKPEN INSTRUCTIONS FOR USE

Instructions for Use

HUMULIN® 70/30 KwikPen®

(insulin isophane human and insulin human)
injectable suspension, for subcutaneous use
3 mL single-patient-use pen (100 units/mL)

Read the Instructions for Use before you start taking HUMULIN 70/30 and each time you get another KwikPen. There may be new information. This information does not take the place of talking to your healthcare provider about your medical condition or your treatment.

Do not share your HUMULIN 70/30 KwikPen with other people, even if the needle has been changed. You may give other people a serious infection or get a serious infection from them.

HUMULIN® 70/30 KwikPen® (“Pen”) is a disposable single-patient-use prefilled pen containing 300 units of HUMULIN 70/30. You can give yourself more than 1 dose from the Pen. Each turn (click) of the Dose Knob dials 1 unit of insulin. You can give from 1 to 60 units in a single injection. If your dose is more than 60 units, you will need to give yourself more than 1 injection. The Plunger only moves a little with each injection, and you may not notice that it moves. The Plunger will only reach the end of the cartridge when you have used all 300 units in the Pen.

People who are blind or have vision problems should not use the Pen without help from a person trained to use the Pen.

How to recognize your HUMULIN 70/30 KwikPen

- Pen color: Beige
- Dose Knob: Brown
- Labels: White label with brown stripe

Supplies you will need to give your injection

- HUMULIN 70/30 KwikPen
- KwikPen compatible Needle (Becton, Dickinson and Company Pen Needles recommended)
- Alcohol swab
- Gauze

Preparing your Pen

- Wash your hands with soap and water.
- Check your Pen to make sure you are taking the right type of insulin. This is especially important if you use more than 1 type of insulin.
- Do not use your Pen past the expiration date printed on the Label or for more than 10 days after you first start using the Pen.
- Always use a new needle for each injection to help prevent infections and blocked needles. Do not reuse or share your needles with other people. You may give other people a serious infection or get a serious infection from them.

Step 1:

- Pull the Pen Cap straight off.
  - Do not remove the Pen Label.
- Wipe the Rubber Seal with an alcohol swab.
  - Do not attach the Needle before mixing.

Step 2:

- Gently roll the Pen between your hands 10 times.

Step 3:

- Move the Pen up and down (invert) 10 times.
  Mixing by rolling and inverting the Pen is important to make sure you get the right dose.

Step 4:

- Check the liquid in the Pen. HUMULIN 70/30 should look white and cloudy after mixing. Do not use if it looks clear or has any lumps or particles in it.

Step 5:

- Select a new Needle.
- Pull off the Paper Tab from the Outer Needle Shield.

Step 6:

- Push the capped Needle straight onto the Pen and twist the Needle on until it is tight.

Step 7:

- Pull off the Outer Needle Shield. Do not throw it away.
- Pull off the Inner Needle Shield and throw it away.

Priming your Pen

Prime before each injection.

- Priming your Pen means removing the air from the Needle and Cartridge that may collect during normal use and ensures that the Pen is working correctly.
- If you do not prime before each injection, you may get too much or too little insulin.

Step 8:

- To prime your Pen, turn the Dose Knob to select 2 units.

Step 9:

- Hold your Pen with the Needle pointing up. Tap the Cartridge Holder gently to collect air bubbles at the top.

Step 10:

- Continue holding your Pen with Needle pointing up. Push the Dose Knob in until it stops, and “0” is seen in the Dose Window. Hold the Dose Knob in and count to 5 slowly.
- You should see insulin at the tip of the Needle.
  - If you do not see insulin, repeat priming steps 8 to 10, no more than 4 times.
  - If you still do not see insulin, change the Needle and repeat priming steps 8 to 10.

Small air bubbles are normal and will not affect your dose.

Selecting your dose

- You can give from 1 to 60 units in a single injection.
- If your dose is more than 60 units, you will need to give more than 1 injection.
  - If you need help with dividing up your dose the right way, ask your healthcare provider.
  - Use a new Needle for each injection and repeat the priming step.

Step 11:

- Turn the Dose Knob to select the number of units you need to inject. The Dose Indicator should line up with your dose.
  - The Pen dials 1 unit at a time.
  - The Dose Knob clicks as you turn it.
  - Do not dial your dose by counting the clicks. You may dial the wrong dose. This may lead to you getting too much insulin or not enough insulin.
  - The dose can be corrected by turning the Dose Knob in either direction until the correct dose lines up with the Dose Indicator.
  - The even numbers (for example, 12) are printed on the dial.
  - The odd numbers, (for example, 25) after the number 1, are shown as full lines.
- Always check the number in the Dose Window to make sure you have dialed the correct dose.

(Example: 12 units shown in the Dose Window)
(Example: 25 units shown in the Dose Window)

- The Pen will not let you dial more than the number of units left in the Pen.
- If you need to inject more than the number of units left in the Pen, you may either:
  - inject the amount left in your Pen and then use a new Pen to give the rest of your dose,
  or
  - get a new Pen and inject the full dose.
- It is normal to see a small amount of insulin left in the Pen that you can not inject.

Giving your injection

- Inject your insulin as your healthcare provider has shown you.
- Change (rotate) your injection sites within the area you choose for each dose to reduce your risk of getting lipodystrophy (pits in skin or thickened skin) and localized cutaneous amyloidosis (skin with lumps) at the injection sites. Do not inject where the skin has pits, is thickened, or has lumps. Do not inject where the skin is tender, bruised, scaly or hard, or into scars or damaged skin.
- Do not try to change your dose while injecting.

Step 12:

- Choose your injection site.
  HUMULIN 70/30 is injected under the skin (subcutaneously) of your stomach area, buttocks, upper legs or upper arms.
- Wipe your skin with an alcohol swab, and let your skin dry before you inject your dose.

Step 13:

- Insert the Needle into your skin.
- Push the Dose Knob all the way in.
- Continue to hold the Dose Knob in and slowly count to 5 before removing the Needle.

Do not try to inject your insulin by turning the Dose Knob. You will not receive your insulin by turning the Dose Knob.

Step 14:

- Pull the Needle out of your skin.
  A drop of insulin at the Needle tip is normal. It will not affect your dose.
- Check the number in the Dose Window.
  - If you see “0” in the Dose Window, you have received the full amount you dialed.
  - If you do not see “0” in the Dose Window, do not redial. Insert the Needle into your skin and finish your injection.
  - If you still do not think you received the full amount you dialed for your injection, do not start over or repeat the injection. Monitor your blood glucose as instructed by your healthcare provider.
  - If you normally need to give 2 injections for your full dose, be sure to give your second injection.

The Plunger only moves a little with each injection, and you may not notice that it moves.
If you see blood after you take the Needle out of your skin, press the injection site lightly with a piece of gauze or an alcohol swab. Do not rub the area.

After your injection

Step 15:

- Carefully replace the Outer Needle Shield.

Step 16:

- Unscrew the capped Needle and throw it away (see Disposing of Pens and Needles section).
- Do not store the Pen with the Needle attached to prevent leaking, blocking the Needle, and air from entering the Pen.

Step 17:

- Replace the Pen Cap by lining up the Cap Clip with the Dose Indicator and pushing straight on.

Disposing of Pens and Needles

- Put your used needles in a FDA-cleared sharps disposal container right away after use. Do not throw away (dispose of) loose needles in your household trash.
- If you do not have a FDA-cleared sharps disposal container, you may use a household container that is:
  - made of a heavy-duty plastic,
  - can be closed with a tight-fitting, puncture-resistant lid, without sharps being able to come out,
  - upright and stable during use,
  - leak-resistant, and
  - properly labeled to warn of hazardous waste inside the container.
- When your sharps disposal container is almost full, you will need to follow your community guidelines for the right way to dispose of your sharps disposal container. There may be state or local laws about how you should throw away used needles and syringes. For more information about safe sharps disposal, and for specific information about sharps disposal in the state that you live in, go to the FDA's website at: http://www.fda.gov/safesharpsdisposal
- Do not dispose of your used sharps disposal container in your household trash unless your community guidelines permit this. Do not recycle your used sharps disposal container.
- The used Pen may be discarded in your household trash after you have removed the needle.

Storing your Pen

Unused Pens

- Store unused Pens in the refrigerator at 36°F to 46°F (2°C to 8°C).
- Do not freeze your insulin. Do not use if it has been frozen.
- Unused Pens may be used until the expiration date printed on the Label, if the Pen has been kept in the refrigerator.

In-use Pen

- Store the Pen you are currently using at room temperature [up to 86°F (30°C)]. Keep away from heat and light.
- Throw away the HUMULIN 70/30 Pen you are using after 10 days, even if it still has insulin left in it.

General information about the safe and effective use of your Pen

- Keep your Pen and needles out of the reach of children.
- Do not use your Pen if any part looks broken or damaged.
- Always carry an extra Pen in case yours is lost or damaged.

Troubleshooting

- If you can not remove the Pen Cap, gently twist the cap back and forth, and then pull the cap straight off.
- If the Dose Knob is hard to push:
  - Pushing the Dose Knob more slowly will make it easier to inject.
  - Your Needle may be blocked. Put on a new Needle and prime the Pen.
  - You may have dust, food, or liquid inside the Pen. Throw the Pen away and get a new Pen.

If you have any questions or problems with your HUMULIN 70/30 KwikPen, contact Lilly at 1-800-LillyRx (1-800-545-5979) or call your healthcare provider for help. For more information on HUMULIN 70/30 KwikPen and insulin, go to www.lilly.com.

Scan this code to launch

www.humulin.com

This Instructions for Use has been approved by the U.S. Food and Drug Administration.

HUMULIN® and HUMULIN® KwikPen® are trademarks of Eli Lilly and Company.

Revised: June 2022

Manufactured by:
Eli Lilly and Company
Indianapolis, IN 46285, USA
US License Number 1891

Copyright © 2013, 2022, Eli Lilly and Company. All rights reserved.

HUMULIN 70/30 KwikPen meets the current dose accuracy and functional requirements of ISO 11608-1.

LIN7030KP-0008-IFU-20220627

PACKAGE CARTON – HUMULIN 70/30 Vial 10 mL

NDC 0002-8715-01

100 units per mL (U-100)

Humulin® 70/30

(insulin isophane human and insulin human)

injectable suspension

10 mL multiple-dose vial

Use only with a U-100 syringe

For subcutaneous use only.

U-100

www.lilly.com

Lilly

PACKAGE LABEL – Humulin 7030 KwikPen 3mL

5 x 3 mL prefilled pens

NDC 0002-8803-59

HP-8803

Humulin® 70/30 KwikPen®

(insulin isophane human and insulin human)

injectable suspension

For Single Patient Use Only

Dispense in this sealed carton

Read Insulin Delivery Device Instructions for Use

For subcutaneous use only.

prefilled insulin delivery device

100 units per mL (U-100)

Needles not included

This device is suitable for use with Becton, Dickinson and Company's insulin pen needles.

Lilly